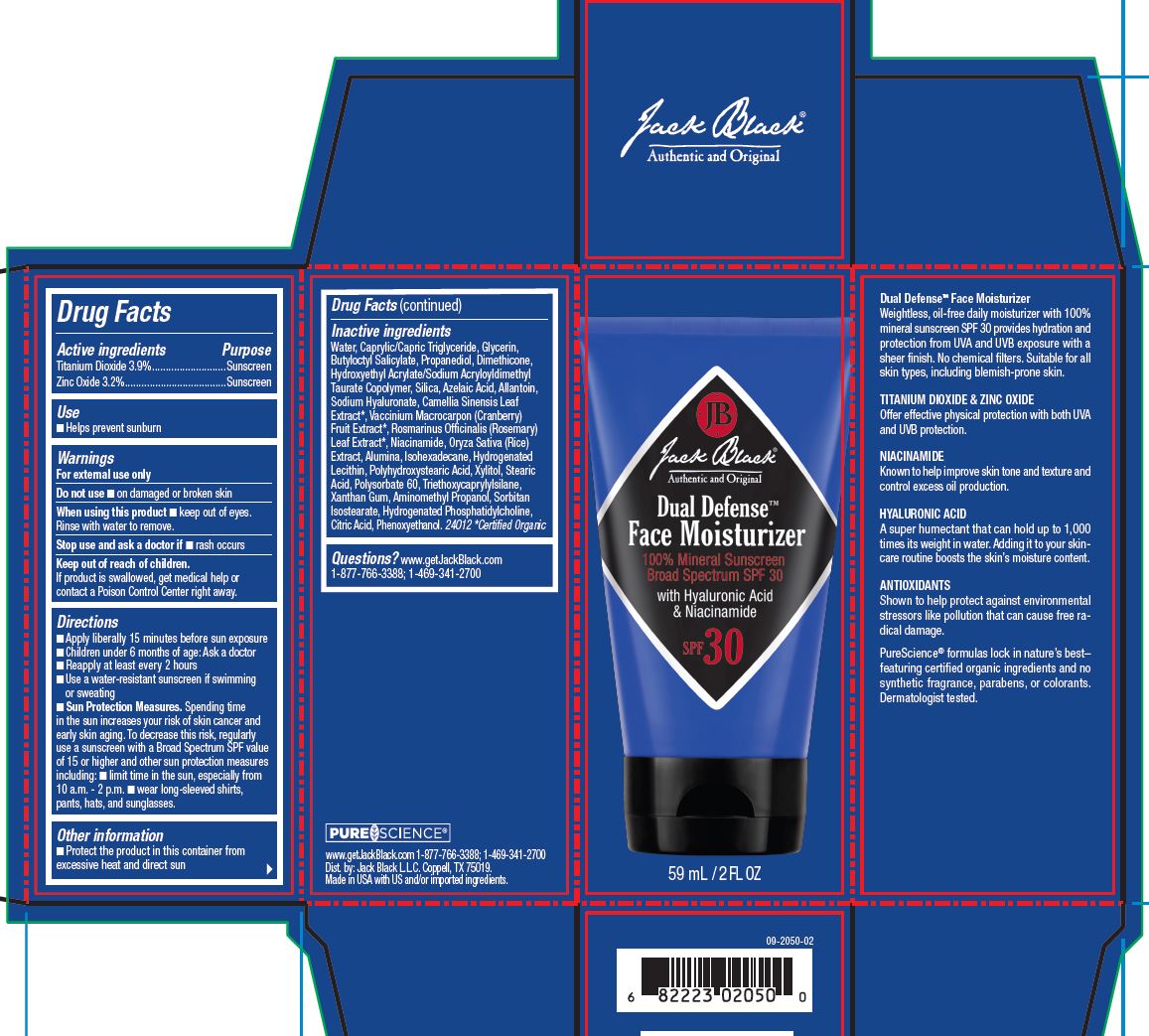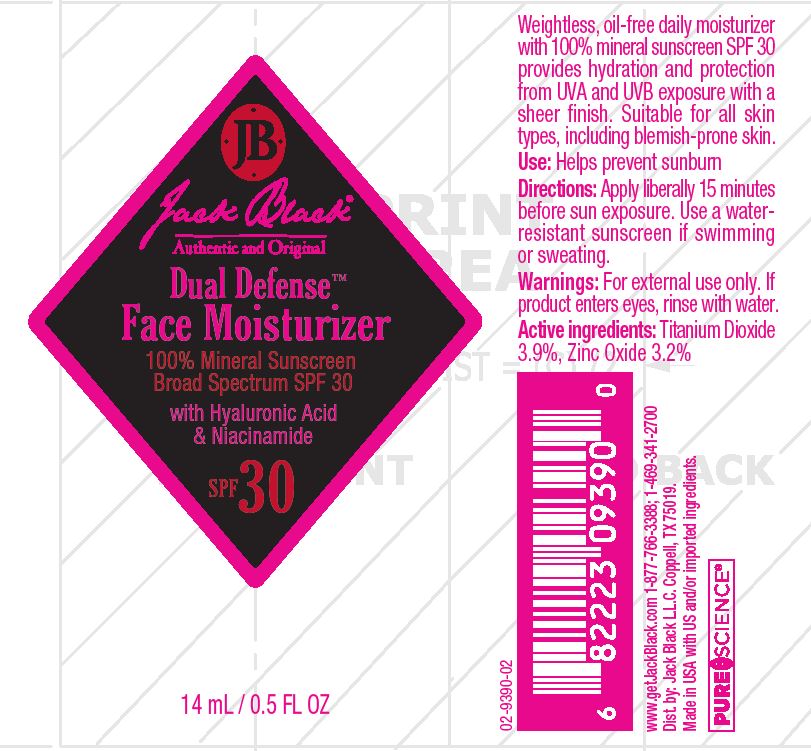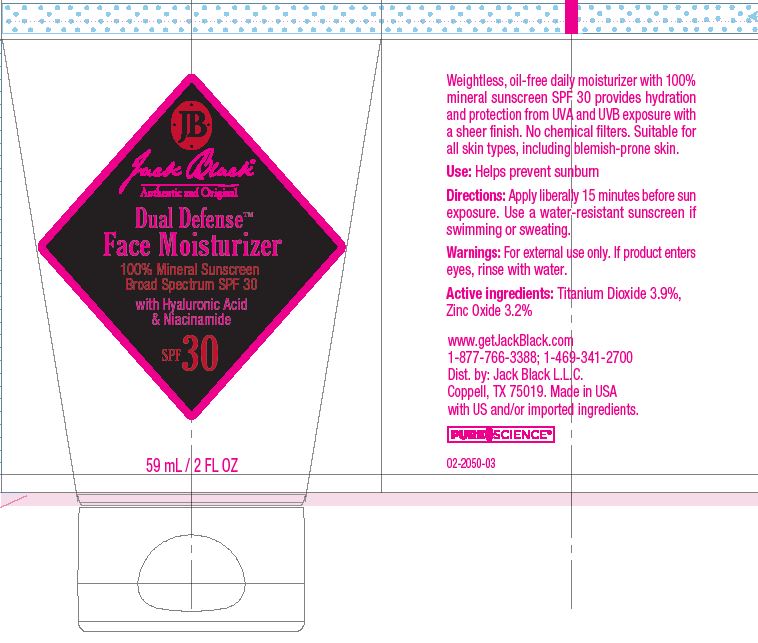 DRUG LABEL: Jack Black
NDC: 66738-502 | Form: LOTION
Manufacturer: Jack Black L.L.C
Category: otc | Type: HUMAN OTC DRUG LABEL
Date: 20240510

ACTIVE INGREDIENTS: TITANIUM DIOXIDE 3.9 g/100 mL; ZINC OXIDE 3.2 g/100 mL
INACTIVE INGREDIENTS: DECAMETHYLTETRASILOXANE; HYDROGENATED SOYBEAN LECITHIN; HYDROXYETHYL ACRYLATE/SODIUM ACRYLOYLDIMETHYL TAURATE COPOLYMER (100000 MPA.S AT 1.5%); ROSEMARY; WATER; ALUMINUM OXIDE; NIACINAMIDE; AZELAIC ACID; MEDIUM-CHAIN TRIGLYCERIDES; GLYCERIN; PROPANEDIOL; SORBITAN ISOSTEARATE; HYDROGENATED SOYBEAN PHOSPHATIDYLCHOLINE; ANHYDROUS CITRIC ACID; XANTHAN GUM; XYLITOL; AMINOMETHYLPROPANOL; SILICON DIOXIDE; PHENOXYETHANOL; TRIETHOXYCAPRYLYLSILANE; HYALURONATE SODIUM; POLYHYDROXYSTEARIC ACID (2300 MW); PEG-60 SORBITAN STEARATE; GREEN TEA LEAF; RICE GERM; ALLANTOIN; BUTYLOCTYL SALICYLATE; ISOHEXADECANE; CRANBERRY; STEARIC ACID

Active Ingredient

Titanium Dioxide 3.9%

Zinc Oxide 3.2%

Purpose

Sunscreen

Use

Helps prevent sunburn

Warnings

For external use only

Do not use • on damaged or broken skin

When using this product • keep out of eyes. Rinse with water to remove.

Stop use and ask a doctor if • rash occurs

Keep out of reach of children. If product is swallowed, get medical help or contact a Poison Control Center right away

Directions

• Apply liberally 15 minutes before sun exposure • Children under 6 months of age: Ask a doctor • Reapply at least every 2 hours • Use a water-resistant sunscreen if swimming or sweating • Sun Protection Measures. Spending time in the sun increases your risk of skin cancer and early skin aging. To decrease this risk, regularly use a sunscreen with a Broad Spectrum SPF value of 15 or higher and other sun protection measures including: • limit time in the sun, especially from 10 a.m. - 2 p.m. • wear long-sleeved shirts, pants, hats, and sunglasses.

Other Information

■ Protect the product in this container from excessive heat and direct sun

Inactive Ingredients

Water, Caprylic/Capric Triglyceride, Glycerin, Butyloctyl Salicylate, Propanediol, Dimethicone, Hydroxyethyl Acrylate/Sodium Acryloyldimethyl Taurate Copolymer, Silica, Azelaic Acid, Allantoin, Sodium Hyaluronate, Camellia Sinensis Leaf Extract*, Vaccinium Macrocarpon (Cranberry) Fruit Extract*, Rosmarinus Officinalis (Rosemary) Leaf Extract*, Niacinamide, Oryza Sativa (Rice) Extract, Alumina, Isohexadecane, Hydrogenated Lecithin, Polyhydroxystearic Acid, Xylitol, Stearic Acid, Polysorbate 60, Triethoxycaprylylsilane, Xanthan Gum, Aminomethyl Propanol, Sorbitan Isostearate, Hydrogenated Phosphatidylcholine, Citric Acid, Phenoxyethanol. 24012 *Certified Organic

Questions?

www.getJackBlack.com 1-877-766-3388; 1-469-341-2700

Principal Display Panel

Jack Black

Authentic and Original

Dual Defense

Face Moisturizer

100% Mineral Sunscreen

Broad Spectrum SPF 30

with Hyaluronic Acid

& Niacinamide

SPF 30

59 mL / 2 FL OZ

Jack Black

Authentic and Original

Dual Defense

Face Moisturizer

100% Mineral Sunscreen

Broad Spectrum SPF 30

with Hyaluronic Acid

& Niacinamide

SPF 30

59 mL / 2 FL OZ

Jack Black

Authentic and Original

Dual Defense

Face Moisturizer

100% Mineral Sunscreen

Broad Spectrum SPF 30

with Hyaluronic Acid

& Niacinamide

SPF 30

15 mL / 0.5 FL OZ